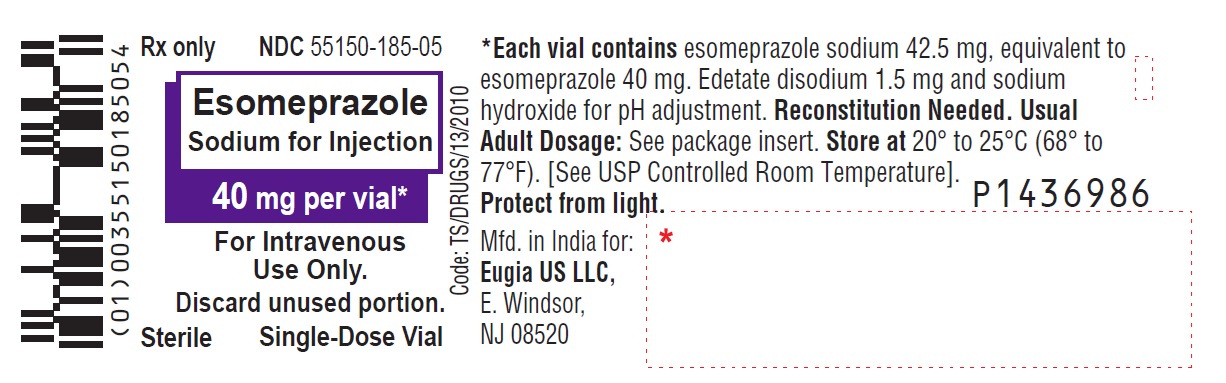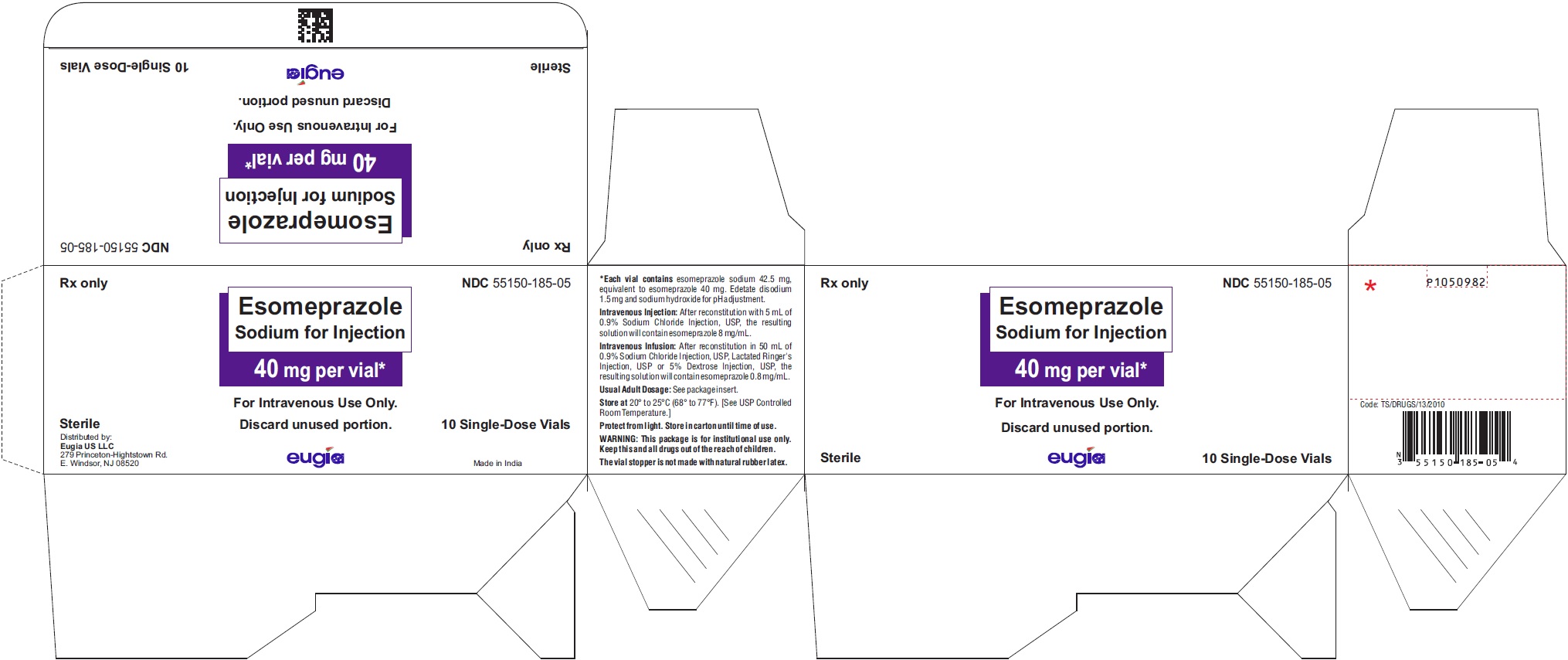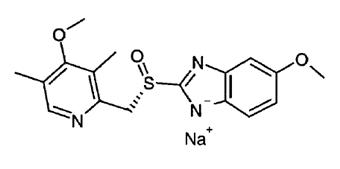 DRUG LABEL: Esomeprazole Sodium
NDC: 55150-185 | Form: INJECTION, POWDER, LYOPHILIZED, FOR SOLUTION
Manufacturer: Eugia US LLC
Category: prescription | Type: Human Prescription Drug Label
Date: 20251107

ACTIVE INGREDIENTS: ESOMEPRAZOLE SODIUM 40 mg/1 1
INACTIVE INGREDIENTS: EDETATE DISODIUM; SODIUM HYDROXIDE; WATER

HIGHLIGHTS OF PRESCRIBING INFORMATION

These highlights do not include all the information needed to use ESOMEPRAZOLE SODIUM FOR INJECTION safely and effectively. See full prescribing information for ESOMEPRAZOLE SODIUM FOR INJECTION.
ESOMEPRAZOLE sodium for injection, for intravenous use
Initial U.S. Approval: 2005

1 INDICATIONS AND USAGE

Esomeprazole sodium for injection is a proton pump inhibitor (PPI) indicated for the:

- Short-term treatment of Gastroesophageal Reflux Disease (GERD) with erosive esophagitis (EE) in adults and pediatric patients 1 month to 17 years of age, as an alternative to oral therapy when oral esomeprazole is not possible or appropriate. (1.1)
- Risk reduction of rebleeding of gastric or duodenal ulcers following therapeutic endoscopy for acute bleeding gastric or duodenal ulcers in adults. (1.2)

2 DOSAGE AND ADMINISTRATION

GERD with Erosive Esophagitis. (2.1):

•The recommended adult dosage is either 20 mg or 40 mg once daily by intravenous injection (no less than 3 minutes) or intravenous infusion (10 minutes to 30 minutes) for up to 10 days.
•The recommended pediatric dosage is based upon age and weight. See full prescribing information.

Risk Reduction of Rebleeding of Gastric and Duodenal Ulcers (2.2):

•The recommended adult dosage is 80 mg administered as an intravenous infusion over 30 minutes, followed by a continuous infusion of 8 mg/hour for a total treatment duration of 72 hours.

Dosage Adjustment for Hepatic Impairment (2.3):

•See full prescribing information for dosage adjustment by severity of impairment and by indication.
Preparation and Administration (2.4, 2.5):

•See full prescribing information for preparation and administration instructions by indication.

3 DOSAGE FORMS AND STRENGTHS

For Injection: 40 mg of esomeprazole as a sterile, freeze-dried, white to off-white, porous cake or lyophilized powder in a single-dose vial for reconstitution. (3)

4 CONTRAINDICATIONS

- Patients with known hypersensitivity to any component of the formulation or to substituted benzimidazoles. (4)
- Patients receiving rilpivirine-containing products. (4, 7)

5 WARNINGS AND PRECAUTIONS

- Gastric Malignancy: In adults, symptomatic response to therapy with esomeprazole sodium for injection does not preclude the presence of gastric malignancy. Consider additional follow-up and diagnostic testing. (5.1)
- Acute Tubulointerstitial Nephritis: Discontinue treatment and evaluate patients. (5.2)
- Clostridium difficile-Associated Diarrhea: PPI therapy may be associated with increased risk. (5.3)
- Bone Fracture: Long-term and multiple daily dose PPI therapy may be associated with an increased risk for osteoporosis-related fractures of the hip, wrist or spine. (5.4)
- Severe Cutaneous Adverse Reactions: Discontinue at the first signs or symptoms of severe cutaneous adverse reactions or other signs of hypersensitivity and consider further evaluation. (5.5)
- Cutaneous and Systemic Lupus Erythematosus: Mostly cutaneous; new onset or exacerbation of existing disease; discontinue esomeprazole sodium for injection and refer to specialist for evaluation. (5.6)
- Interaction with Clopidogrel: Avoid concomitant use of esomeprazole sodium for injection. (5.7, 7)
- Hypomagnesemia and Mineral Metabolism: Reported rarely with prolonged treatment with PPIs. (5.8)
- Interaction with St. John’s Wort or Rifampin: Avoid concomitant use of esomeprazole sodium for injection. (5.9, 7)
- Interactions with Diagnostic Investigations for Neuroendocrine Tumors: Increased chromogranin A (CgA) levels may interfere with diagnostic investigations for neuroendocrine tumors; temporarily stop esomeprazole sodium for injection at least 14 days before assessing CgA levels. (5.10, 7)
- Interaction with Methotrexate: Concomitant use with PPIs may elevate and/or prolong serum concentrations of methotrexate and/or its metabolite, possibly leading to toxicity. With high dose methotrexate administration, consider a temporary withdrawal of esomeprazole sodium for injection. (5.11, 7)
- Fundic Gland Polyps: Risk increases with long-term use, especially beyond one year. Use the shortest duration of therapy. (5.12)

6 ADVERSE REACTIONS

Most common adverse reactions (≥1%) are: headache, flatulence, nausea, abdominal pain, injection site reaction, diarrhea, dry mouth, dizziness/vertigo, constipation and pruritus. (6.1)
To report SUSPECTED ADVERSE REACTIONS, contact Eugia US LLC at 1-866-850-2876 or FDA at 1-800-FDA-1088 or www.fda.gov/medwatch.

7 DRUG INTERACTIONS

See full prescribing information for a list of clinically important drug interactions. (7)

FULL PRESCRIBING INFORMATION

1 INDICATIONS AND USAGE

1.1 Treatment of Gastroesophageal Reflux Disease (GERD) with Erosive Esophagitis (EE)

Esomeprazole sodium for injection is indicated for the short-term treatment of GERD with EE in adults and pediatric patients 1 month to 17 years, inclusively as an alternative to oral therapy when oral esomeprazole is not possible or appropriate.

1.2 Risk Reduction of Rebleeding of Gastric or Duodenal Ulcers following Therapeutic Endoscopy in Adults

Esomeprazole sodium for injection is indicated for risk reduction of rebleeding of gastric or duodenal ulcers following therapeutic endoscopy for acute bleeding gastric or duodenal ulcers in adults.

2 DOSAGE AND ADMINISTRATION

2.1 Dosage for GERD with EE

Adult Patients

The recommended adult dosage is either 20 mg or 40 mg esomeprazole sodium for injection given once daily by intravenous injection (over at least 3 minutes) or intravenous infusion (10 minutes to 30 minutes) for up to 10 days [see Dosage and Administration (2.4)].

Pediatric Patients

The recommended dosage for pediatric patients is based on age and body weight as shown in Table 1 below. Administer as an intravenous infusion over 10 to 30 minutes once daily for up to 10 days [see Dosage and Administration (2.4)].

Table 1: Recommended Pediatric Dosage Regimen for GERD with EE
Age and Body Weight |  | Dosage Regimen
1 month to less than 1 year of age |  | 0.5 mg/kg once daily
1 year to 17 years | less than 55 kg | 10 mg once daily
1 year to 17 years | 55 kg or greater | 20 mg once daily

Completion of Treatment

- The safety and effectiveness of esomeprazole sodium for injection for more than 10 days have not been demonstrated.
- As soon as oral therapy is possible or appropriate, discontinue intravenous therapy with esomeprazole sodium for injection and continue with oral esomeprazole therapy.

2.2 Dosage for Risk Reduction of Rebleeding of Gastric or Duodenal Ulcers following Therapeutic Endoscopy in Adults

The recommended adult dosage is 80 mg esomeprazole sodium for injection administered as an intravenous infusion over 30 minutes followed by a continuous infusion of 8 mg/hour for a total treatment duration of 72 hours (i.e., includes initial 30-minute loading dose plus 71.5 hours of continuous infusion) [see Dosage and Administration (2.5)].
Intravenous therapy is aimed solely at the acute initial management of bleeding gastric or duodenal ulcers and does not constitute full treatment. Administer oral acid-suppressive therapy following intravenous therapy for a full course of treatment.

2.3 Dosage Adjustment for Hepatic Impairment

GERD with EE
For patients with severe hepatic impairment (Child-Pugh Class C), the maximum dosage is 20 mg once daily [see Use in Specific Populations (8.6)].
Risk Reduction of Rebleeding of Gastric or Duodenal Ulcers following Therapeutic Endoscopy in Adults
For patients with mild to moderate hepatic impairment (Child-Pugh Classes A and B, respectively), administered 80 mg as an intravenous infusion over 30 minutes, followed by a continuous infusion of 6 mg/hour for 71.5 hours.
For patients with severe hepatic impairment (Child-Pugh Class C), administered 80 mg as an intravenous infusion over 30 minutes, followed by a continuous infusion of 4 mg/hour for 71.5 hours [see Use in Specific Populations (8.6)].

2.4 Preparation and Administration Instructions for GERD with EE

Do not administer esomeprazole sodium for injection concomitantly with any other medications through the same intravenous site and/or tubing.
Oral antacids may be used during treatment with esomeprazole sodium for injection.
Intravenous Injection Over At Least 3 Minutes in Adult Patients

1. Reconstitute esomeprazole sodium for injection with 5 mL of 0.9% Sodium Chloride Injection, USP.
2. Withdraw the desired dose of the reconstituted esomeprazole sodium for injection solution for a 20 mg or 40 mg dose.
3. Discard any unused portion of esomeprazole sodium for injection solution remaining in the vial.
4. Inspect the reconstituted esomeprazole sodium for injection solution visually for particulate matter and discoloration prior to and during administration.
5. Administer as an intravenous injection over no less than 3 minutes.
6. Flush the intravenous line with either 0.9% Sodium Chloride Injection, USP, Lactated Ringer’s Injection, USP or 5% Dextrose Injection, USP both prior to and after administration of esomeprazole sodium for injection.

Intravenous Infusion Over 10 Minutes to 30 Minutes in Adult and Pediatric Patients

1. Reconstitute the contents of one vial of esomeprazole sodium for injection with 5 mL of 0.9% Sodium Chloride Injection, USP, Lactated Ringer’s Injection, USP or 5% Dextrose Injection, USP.
2. Further dilute the resulting solution with 45 mL of 0.9% Sodium Chloride Injection, USP, Lactated Ringer’s Injection, USP or 5% Dextrose Injection, USP to a final concentration of 0.8 mg/mL.
3. Withdraw the desired dose of the reconstituted esomeprazole sodium for injection solution for an adult or pediatric dose.
4. Discard any unused portion of esomeprazole sodium for injection solution remaining in the vial.
5. Inspect the reconstituted esomeprazole sodium for injection solution visually for particulate matter and discoloration prior to and during administration.
6. Administer intravenously over 10 minutes to 30 minutes.
7. Flush the intravenous line with either 0.9% Sodium Chloride Injection, USP, Lactated Ringer’s Injection, USP or 5% Dextrose Injection, USP both prior to and after administration of esomeprazole sodium for injection.

Storage
Store the final (diluted) esomeprazole sodium for injection solution at room temperature up to 30°C (86°F) and administer within the designated time period as listed in Table 2 below.

Table 2: Storage Time for Final (diluted) Esomeprazole Sodium for Injection Solution
Diluent | Administer within:
0.9% Sodium Chloride Injection, USP | 12 hours
Lactated Ringer’s Injection, USP | 12 hours
5% Dextrose Injection, USP | 6 hours

2.5 Preparation and Administration Instructions for Risk Reduction of Rebleeding of Gastric or Duodenal Ulcers in Adults

Do not administer esomeprazole sodium for injection concomitantly with any other medications through the same intravenous site and/or tubing.
Oral antacids may be used during treatment with esomeprazole sodium for injection.
Loading Dose (80 mg)

1. Reconstitute each of two 40 mg vials of esomeprazole sodium for injection with 5 mL of 0.9% Sodium Chloride Injection, USP.
2. Further dilute the resulting solution in 100 mL 0.9% Sodium Chloride Injection, USP.
3. Inspect the reconstituted esomeprazole sodium for injection solution visually for particulate matter and discoloration prior to and during administration.
4. Administer intravenously over 30 minutes.
5. Flush the intravenous line with either 0.9% Sodium Chloride Injection, USP, Lactated Ringer’s Injection, USP or 5% Dextrose Injection, USP both prior to and after administration of esomeprazole sodium for injection.

Continuous Infusion

1. Reconstitute each of two 40 mg vials of esomeprazole sodium for injection with 5 mL of 0.9% Sodium Chloride Injection, USP.
2. Further dilute the reconstituted esomeprazole sodium for injection solution in 100 mL 0.9% Sodium Chloride Injection, USP.
3. Inspect the reconstituted esomeprazole sodium for injection solution visually for particulate matter and discoloration prior to and during administration.
4. Administer intravenously as a continuous infusion at a rate of 8 mg/hour for 71.5 hours.
5. Flush the intravenous line with either 0.9% Sodium Chloride Injection, USP, Lactated Ringer’s Injection, USP or 5% Dextrose Injection, USP both prior to and after administration of esomeprazole sodium for injection.

Storage

- Store the final (diluted) esomeprazole sodium for injection solution at room temperature up to 30°C (86°F) and administer within 12 hours.

3 DOSAGE FORMS AND STRENGTHS

For Injection: 40 mg of esomeprazole as a sterile, freeze-dried, white to off-white, porous cake or lyophilized powder in a single-dose vial for reconstitution.

4 CONTRAINDICATIONS

- Esomeprazole sodium for injection is contraindicated in patients with known hypersensitivity to substituted benzimidazoles or to any component of the formulation. Hypersensitivity reactions may include anaphylaxis, anaphylactic shock, angioedema, bronchospasm, acute tubulointerstitial nephritis, and urticaria [see Warnings and Precautions (5.2), Adverse Reactions (6.2)].
- Proton pump inhibitors (PPIs), including esomeprazole sodium for injection, are contraindicated in patients receiving rilpivirine-containing products [see Drug Interactions (7)].

5 WARNINGS AND PRECAUTIONS

5.1 Presence of Gastric Malignancy

In adults, symptomatic response to therapy with esomeprazole sodium for injection does not preclude the presence of gastric malignancy. Consider additional follow-up and diagnostic testing in adult patients who have suboptimal response or an early symptomatic relapse after completing treatment with a PPI. In older patients also consider an endoscopy.

5.2 Acute Tubulointerstitial Nephritis

Acute tubulointerstitial nephritis (TIN) has been observed in patients taking PPIs and may occur at any point during PPI therapy. Patients may present with varying signs and symptoms from symptomatic hypersensitivity reactions to non-specific symptoms of decreased renal function (e.g., malaise, nausea, anorexia). In reported case series, some patients were diagnosed on biopsy and in the absence of extra-renal manifestations (e.g., fever, rash or arthralgia). Discontinue esomeprazole sodium for injection and evaluate patients with suspected acute TIN [see Contraindications (4)].

5.3 Clostridium difficile-Associated Diarrhea

Published observational studies suggest that PPI therapy like esomeprazole sodium for injection may be associated with an increased risk of Clostridium difficile-associated diarrhea, especially in hospitalized patients. This diagnosis should be considered for diarrhea that does not improve [see Adverse Reactions (6.2)].
Patients should use the lowest dose and shortest duration of PPI therapy appropriate to the condition being treated.

5.4 Bone Fracture

Several published observational studies suggest that proton pump inhibitor (PPI) therapy may be associated with an increased risk for osteoporosis-related fractures of the hip, wrist, or spine. The risk of fracture was increased in patients who received high-dose, defined as multiple daily doses, and long-term PPI therapy (a year or longer). Patients should use the lowest dose and shortest duration of PPI therapy appropriate to the condition being treated. Patients at risk for osteoporosis-related fractures should be managed according to established treatment guidelines [see Dosage and Administration (2.1, 2.2), Adverse Reactions (6.2)].

5.5 Severe Cutaneous Adverse Reactions

Severe cutaneous adverse reactions, including Stevens-Johnson syndrome (SJS) and toxic epidermal necrolysis (TEN), drug reaction with eosinophilia and systemic symptoms (DRESS), and acute generalized exanthematous pustulosis (AGEP) have been reported in association with the use of PPIs [see Adverse Reactions (6.2)]. Discontinue esomeprazole sodium for injection at the first signs or symptoms of severe cutaneous adverse reactions or other signs of hypersensitivity and consider further evaluation.

5.6 Cutaneous and Systemic Lupus Erythematosus

Cutaneous lupus erythematosus (CLE) and systemic lupus erythematosus (SLE) have been reported in patients taking PPIs, including esomeprazole. These events have occurred as both new onset and an exacerbation of existing autoimmune disease. The majority of PPI-induced lupus erythematosus cases were CLE.
The most common form of CLE reported in patients treated with PPIs was subacute CLE (SCLE) and occurred within weeks to years after continuous drug therapy in patients ranging from infants to the elderly. Generally, histological findings were observed without organ involvement.
Systemic lupus erythematosus (SLE) is less commonly reported than CLE in patients receiving PPIs. PPI associated SLE is usually milder than non-drug induced SLE. Onset of SLE typically occurred within days to years after initiating treatment primarily in patients ranging from young adults to the elderly. The majority of patients presented with rash; however, arthralgia and cytopenia were also reported.
Avoid administration of PPIs for longer than medically indicated. If signs or symptoms consistent with CLE or SLE are noted in patients receiving esomeprazole sodium for injection, discontinue the drug and refer the patient to the appropriate specialist for evaluation. Most patients improve with discontinuation of the PPI alone in 4 to 12 weeks. Serological testing (e.g., ANA) may be positive and elevated serological test results may take longer to resolve than clinical manifestations.

5.7 Interaction with Clopidogrel

Avoid concomitant use of esomeprazole sodium for injection with clopidogrel. Clopidogrel is a prodrug. Inhibition of platelet aggregation by clopidogrel is entirely due to an active metabolite. The metabolism of clopidogrel to its active metabolite can be impaired by use with concomitant medications, such as esomeprazole, that inhibit CYP2C19 activity. Concomitant use of clopidogrel with 40 mg esomeprazole reduces the pharmacological activity of clopidogrel. When using esomeprazole sodium for injection consider alternative anti-platelet therapy [see Drug Interactions (7)].

5.8 Hypomagnesemia and Mineral Metabolism

Hypomagnesemia, symptomatic and asymptomatic, has been reported rarely in patients treated with PPIs for at least three months, in most cases after a year of therapy. Serious adverse events include tetany, arrhythmias, and seizures. Hypomagnesemia may lead to hypocalcemia and/or hypokalemia and may exacerbate underlying hypocalcemia in at-risk patients. In most patients, treatment of hypomagnesemia required magnesium replacement and discontinuation of the PPI.
For patients expected to be on prolonged treatment or who take PPIs with medications such as digoxin or drugs that may cause hypomagnesemia (e.g., diuretics), health care professionals may consider monitoring magnesium levels prior to initiation of PPI treatment and periodically [see Adverse Reactions (6.2)].
Consider monitoring magnesium and calcium levels prior to initiation of esomeprazole sodium for injection and periodically while on treatment in patients with a preexisting risk of hypocalcemia (e.g., hypoparathyroidism). Supplement with magnesium and/or calcium, as necessary. If hypocalcemia is refractory to treatment, consider discontinuing the PPI.

5.9 Interaction with St. John's Wort or Rifampin

Drugs which induce CYP2C19 or CYP3A4 (such as St. John’s Wort or rifampin) can substantially decrease esomeprazole concentrations [see Drug Interactions (7)]. Avoid concomitant use of esomeprazole sodium for injection with St. John’s Wort or rifampin.

5.10 Interactions with Diagnostic Investigations for Neuroendocrine Tumors

Serum chromogranin A (CgA) levels increase secondary to drug-induced decreases in gastric acidity. The increased CgA level may cause false positive results in diagnostic investigations for neuroendocrine tumors. Healthcare providers should temporarily stop esomeprazole treatment at least 14 days before assessing CgA levels and consider repeating the test if initial CgA levels are high. If serial tests are performed (e.g., for monitoring), the same commercial laboratory should be used for testing, as reference ranges between tests may vary [see Drug Interactions (7)].

5.11 Interaction with Methotrexate

Literature suggests that concomitant use of PPIs with methotrexate (primarily at high dose; see methotrexate prescribing information) may elevate and prolong serum levels of methotrexate and/or its metabolite, possibly leading to methotrexate toxicities. In high-dose methotrexate administration, a temporary withdrawal of the PPI may be considered in some patients [see Drug Interactions (7)].

5.12 Fundic Gland Polyps

PPI use is associated with an increased risk of fundic gland polyps that increases with long-term use, especially beyond one year. Most PPI users who developed fundic gland polyps were asymptomatic and fundic gland polyps were identified incidentally on endoscopy. Use the shortest duration of PPI therapy appropriate to the condition being treated.

6 ADVERSE REACTIONS

The following serious adverse reactions are described below and elsewhere in labeling:

- Acute Tubulointerstitial Nephritis [see Warnings and Precautions (5.2)]
- Clostridium difficile-Associated Diarrhea [see Warnings and Precautions (5.3)]
- Bone Fracture [see Warnings and Precautions (5.4)]
- Severe Cutaneous Adverse Reactions [see Warnings and Precautions (5.5)]
- Cutaneous and Systemic Lupus Erythematosus [see Warnings and Precautions (5.6)]
- Hypomagnesemia and Mineral Metabolism [see Warnings and Precautions (5.8)]
- Fundic Gland Polyps [see Warnings and Precautions (5.12)]

6.1 Clinical Trials Experience

Because clinical trials are conducted under widely varying conditions, adverse reaction rates observed in the clinical trials of a drug cannot be directly compared to rates in the clinical trials of another drug and may not reflect the rates observed in practice.
Symptomatic GERD and EE
Adults
The safety of esomeprazole sodium for injection is based on results from clinical trials conducted in four different populations including healthy subjects (n=204) and patients with bleeding gastric or duodenal ulcers (n=375).
The data described below reflect exposure to esomeprazole sodium for injection in 359 patients in actively-controlled trials: symptomatic GERD with or without a history of EE (n=199) and patients with EE (n=160). The population was 18 to 77 years of age; 45% Male, 52% Caucasian, 17% Black, 3% Asian, and 28% other race. Most patients received doses of either 20 or 40 mg either as an infusion or an injection. Adverse reactions occurring in at least 1% of patients are listed below in Table 3:

Table 3: Adverse Reactions^1 in the Esomeprazole Sodium for Injection Group in Active Controlled Trials of Symptomatic GERD with or without EE
Adverse Reactions | % of patients Esomeprazole sodium for injection (n=359)
Headache | 11
Flatulence | 10
Nausea | 6
Abdominal pain | 6
Diarrhea | 4
Mouth dry | 4
Dizziness/vertigo | 3
Constipation | 3
Injection site reaction | 2
Pruritus | 1
^1 Incidence of at least 1% in the Esomeprazole sodium for injection group

Intravenous treatment with esomeprazole sodium for injection 20 and 40 mg-administered as an injection or as an infusion was found to have a safety profile similar to that of oral esomeprazole.
Pediatrics
A randomized, open-label, multi-national study to evaluate the pharmacokinetics of repeated intravenous doses of once daily esomeprazole sodium for injection in pediatric patients 1 month to 17 years old, inclusive was performed [see Clinical Pharmacology (12.3)]. The safety results are consistent with the known safety profile of esomeprazole and no unexpected safety signals were identified.
Risk Reduction of Rebleeding of Gastric or Duodenal Ulcers in Adults
The data described in Table 4 below reflect exposure to esomeprazole sodium for injection in 375 patients who presented with endoscopically confirmed gastric or duodenal ulcer bleeding in a placebo-controlled trial. The population was 18 to 98 years old; 68% Male, 87% Caucasian, 1% Black, 7% Asian, and 4% other race. Following endoscopic hemostasis, patients received either placebo or 80 mg esomeprazole sodium for injection as an intravenous infusion over 30 minutes followed by a continuous infusion of 8 mg/hour for a total treatment duration of 72 hours. After the initial 72-hour period, all patients received an oral PPI for 27 days.

Table 4: Adverse Reactions^1 Occurring within 72 Hours after Start of Treatment in Patients with Endoscopically Confirmed Bleeding Ulcers
 | % of patients
 | Esomeprazole sodium for injection (n=375) | Placebo (n=389)
Duodenal ulcer hemorrhage | 4 | 4
Injection site reaction^2 | 4 | 1
Pyrexia | 4 | 3
Cough | 1 | 0.3
Dizziness | 1 | 1
^1. Incidence ≥1% in the esomeprazole sodium for injection group and greater than placebo group
^2. Injection site reactions included erythema, swelling, inflammation, pruritus, phlebitis, thrombophlebitis and superficial phlebitis.

With the exception of injection site reactions described above, intravenous treatment with esomeprazole sodium for injection administered as an injection or as an infusion was found to have a safety profile similar to that of oral esomeprazole.

6.2 Postmarketing Experience

The following adverse reactions have been identified during post-approval use of esomeprazole. Because these reactions are reported voluntarily from a population of uncertain size, it is not always possible to reliably estimate their frequency or establish a causal relationship to drug exposure.
Blood and Lymphatic System Disorders: agranulocytosis, pancytopenia;
Eye Disorders: blurred vision;
Gastrointestinal Disorders: pancreatitis; stomatitis; microscopic colitis; fundic gland polyps;
Hepatobiliary Disorders: hepatic failure, hepatitis with or without jaundice;
Immune System Disorders: anaphylactic reaction/shock; systemic lupus erythematosus;
Infections and Infestations: GI candidiasis;
Metabolism and nutritional disorders: hypomagnesemia (may lead to hypocalcemia and/or hypokalemia) [see Warnings and Precautions (5.8)], hyponatremia;
Musculoskeletal and Connective Tissue Disorders: muscular weakness, myalgia, bone fracture;
Nervous System Disorders: hepatic encephalopathy, taste disturbance;
Psychiatric Disorders: aggression, agitation, depression, hallucination;
Renal and Urinary Disorders: interstitial nephritis;
Reproductive System and Breast Disorders: gynecomastia, erectile dysfunction;
Respiratory, Thoracic and Mediastinal Disorders: bronchospasm;
Skin and Subcutaneous Tissue Disorders: alopecia, erythema multiforme, hyperhidrosis, photosensitivity, Stevens-Johnson syndrome, toxic epidermal necrolysis (TEN, some fatal), drug reaction with eosinophilia and systemic symptoms (DRESS), and acute generalized exanthematous pustulosis (AGEP), cutaneous lupus erythematosus.
Adverse reactions associated with omeprazole may also be expected to occur with esomeprazole sodium for injection. See the full prescribing information for oral omeprazole for complete safety information.

7 DRUG INTERACTIONS

Tables 5 and 6 include drugs with clinically important drug interactions and interaction with diagnostics when administered concomitantly with esomeprazole and instructions for preventing or managing them.
Consult the labeling of concomitantly used drugs to obtain further information about interactions with PPIs.

Table 5: Clinically Relevant Interactions Affecting Drugs Co-Administered with Esomeprazole and Interaction with Diagnostics
Antiretrovirals
Clinical Impact: | The effect of PPIs on antiretroviral drugs is variable. The clinical importance and the mechanisms behind these interactions are not always known.; - Decreased exposure of some antiretroviral drugs (e.g., rilpivirine atazanavir, and nelfinavir) when used concomitantly with esomeprazole may reduce antiviral effect and promote the development of drug resistance [see Clinical Pharmacology (12.3)].; - Increased exposure of other antiretroviral drugs (e.g., saquinavir) when used concomitantly with esomeprazole may increase toxicity [see Clinical Pharmacology (12.3)].; - There are other antiretroviral drugs which do not result in clinically relevant interactions with esomeprazole.
Intervention: | Rilpivirine-containing products: Concomitant use with esomeprazole sodium for injection is contraindicated [see Contraindications (4)]. Atazanavir: See prescribing information for atazanavir for dosing information. Nelfinavir: Avoid concomitant use with esomeprazole sodium for injection. See prescribing information for nelfinavir. Saquinavir: See the prescribing information for saquinavir for monitoring of potential saquinavir-related toxicities. Other antiretrovirals: See prescribing information for specific antiretroviral drugs
Warfarin
Clinical Impact: | Increased INR and prothrombin time in patients receiving PPIs, including esomeprazole, and warfarin concomitantly. Increases in INR and prothrombin time may lead to abnormal bleeding and even death.
Intervention: | Monitor INR and prothrombin time and adjust the dose of warfarin, if needed, to maintain the target INR range.
Methotrexate
Clinical Impact: | Concomitant use of esomeprazole with methotrexate (primarily at high dose) may elevate and prolong serum concentrations of methotrexate and/or its metabolite hydroxymethotrexate, possibly leading to methotrexate toxicities. No formal drug interaction studies of high-dose methotrexate with PPIs have been conducted [see Warnings and Precautions (5.11)].
Intervention: | A temporary withdrawal of esomeprazole sodium for injection may be considered in some patients receiving high-dose methotrexate.
2C19 Substrates (e.g., clopidogrel, citalopram, cilostazol, diazepam)
Clopidogrel
Clinical Impact: | Concomitant use of esomeprazole 40 mg resulted in reduced plasma concentrations of the active metabolite of clopidogrel and a reduction in platelet inhibition [see Clinical Pharmacology (12.3)]. There are no adequate combination studies of a lower dose of esomeprazole or a higher dose of clopidogrel in comparison with the approved dose of clopidogrel.
Intervention: | Avoid concomitant use with esomeprazole sodium for injection. Consider use of alternative anti-platelet therapy [see Warnings and Precautions (5.7)].
Citalopram
Clinical Impact: | Increased exposure of citalopram leading to an increased risk of QT prolongation [see Clinical Pharmacology (12.3)].
Intervention: | Limit the dose of citalopram to a maximum of 20 mg per day. See prescribing information for citalopram.
Cilostazol
Clinical Impact: | Increased exposure of cilostazol and one of its active metabolites (3,4-dihydro-cilostazol) [see Clinical Pharmacology (12.3)].
Intervention: | Consider reducing the dose of cilostazol to 50 mg twice daily. See prescribing information for cilostazol.
Digoxin
Clinical Impact: | Potential for increased exposure of digoxin [see Clinical Pharmacology (12.3)].
Intervention: | Monitor digoxin concentrations and adjust the dose, if needed, to maintain therapeutic drug concentrations. See prescribing information for digoxin.
Drugs Dependent on Gastric pH for Absorption (e.g., iron salts, erlotinib, dasatinib, nilotinib, mycophenolate mofetil, ketoconazole/itraconazole)
Clinical Impact: | Esomeprazole can reduce the absorption of other drugs due to its effect on reducing intragastric acidity
Intervention: | Mycophenolate mofetil (MMF): Co-administration of omeprazole, of which esomeprazole is an enantiomer, in healthy subjects and in transplant patients receiving MMF has been reported to reduce the exposure to the active metabolite, mycophenolic acid (MPA), possibly due to a decrease in MMF solubility at an increased gastric pH. The clinical relevance of reduced MPA exposure on organ rejection has not been established in transplant patients receiving esomeprazole sodium for injection and MMF. Use esomeprazole sodium for injection with caution in transplant patients receiving MMF [see Clinical Pharmacology (12.3)]. See the prescribing information for other drugs dependent on gastric pH for absorption.
Tacrolimus
Clinical Impact: | Potentially increased exposure of tacrolimus, especially in transplant patients who are intermediate or poor metabolizers of CYP2C19.
Intervention: | Monitor tacrolimus whole blood concentrations and consider reducing the dose, if needed, to maintain therapeutic drug concentrations. See prescribing information for tacrolimus.
Interactions with Investigations of Neuroendocrine Tumors
Clinical Impact: | Serum chromogranin A (CgA) levels increase secondary to PPI-induced decreases in gastric acidity. The increased CgA level may cause false positive results in diagnostic investigations for neuroendocrine tumors [see Warnings and Precautions (5.10), Clinical Pharmacology (12.2)].
Intervention: | Discontinue esomeprazole sodium for injection at least 14 days before assessing CgA levels and consider repeating the test if initial CgA levels are high. If serial tests are performed (e.g. for monitoring), the same commercial laboratory should be used for testing, as reference ranges between tests may vary.
Interaction with Secretin Stimulation Test
Clinical Impact: | Hyper-response in gastrin secretion in response to secretin stimulation test, falsely suggesting gastrinoma.
Intervention: | Discontinue esomeprazole sodium for injection 4 weeks prior to testing [see Clinical Pharmacology (12.2)]

Table 6: Clinically Relevant Interactions Affecting Esomeprazole When Co-Administered with Other Drugs
CYP2C19 or CYP3A4 Inducers
Clinical Impact: | Decreased exposure of esomeprazole when used concomitantly with strong inducers [see Clinical Pharmacology (12.3)].
Intervention: | St. John’s Wort, rifampin: Avoid concomitant use with esomeprazole sodium for injection [see Warnings and Precautions (5.9)]. Ritonavir-containing products: see prescribing information for specific drugs
Voriconazole
Clinical Impact: | Increased exposure of esomeprazole [see Clinical Pharmacology (12.3)].
Intervention: | Dose adjustment of esomeprazole sodium for injection is not normally required. See prescribing information for voriconazole.

8 USE IN SPECIFIC POPULATIONS

8.1 Pregnancy

Risk Summary
There are no adequate and well-controlled studies with esomeprazole in pregnant women. Esomeprazole is the s-isomer of omeprazole. Available epidemiologic data fail to demonstrate an increased risk of major congenital malformations or other adverse pregnancy outcomes with first trimester omeprazole use. Reproduction studies in rats and rabbits resulted in dose-dependent embryo-lethality at omeprazole doses that were approximately 3.4 to 34 times an oral human dose of 40 mg (based on a body surface area for a 60 kg person).
Teratogenicity was not observed in animal reproduction studies with administration of oral esomeprazole magnesium in rats and rabbits with doses about 68 times and 42 times, respectively, an oral human dose of 40 mg (based on a body surface area basis for a 60 kg person). Changes in bone morphology were observed in offspring of rats dosed through most of pregnancy and lactation at doses equal to or greater than approximately 34 times an oral human dose of 40 mg. When maternal administration was confined to gestation only, there were no effects on bone physeal morphology in the offspring at any age (see Data).
The estimated background risks of major birth defects and miscarriage for the indicated population are unknown. All pregnancies have a background risk of birth defect, loss or other adverse outcomes. In the U.S. general population, the estimated background risk of major birth defects and miscarriage in clinically recognized pregnancies is 2% to 4% and 15% to 20%, respectively.
Data
Human Data
Esomeprazole is the S-isomer of omeprazole. Four epidemiological studies compared the frequency of congenital abnormalities among infants born to women who used omeprazole during pregnancy with the frequency of abnormalities among infants of women exposed to H2-receptor antagonists or other controls.
A population based retrospective cohort epidemiological study from the Swedish Medical Birth Registry, covering approximately 99% of pregnancies, from 1995 to 99, reported on 955 infants (824 exposed during the first trimester with 39 of these exposed beyond first trimester, and 131 exposed after the first trimester) whose mothers used omeprazole during pregnancy. The number of infants exposed in utero to omeprazole that had any malformation, low birth weight, low Apgar score, or hospitalization was similar to the number observed in this population. The number of infants born with ventricular septal defects and the number of stillborn infants was slightly higher in the omeprazole-exposed infants than the expected number in this population.
A population-based retrospective cohort study covering all live births in Denmark from 1996 to 2009, reported on 1,800 live births whose mothers used omeprazole during the first trimester of pregnancy and 837,317 live births whose mothers did not use any proton pump inhibitor. The overall rate of birth defects in infants born to mothers with first trimester exposure to omeprazole was 2.9% and 2.6% in infants born to mothers not exposed to any proton pump inhibitor during the first trimester.
A retrospective cohort study reported on 689 pregnant women exposed to either H2-blockers or omeprazole in the first trimester (134 exposed to omeprazole) and 1,572 pregnant women unexposed to either during the first trimester. The overall malformation rate in offspring born to mothers with first trimester exposure to omeprazole, an H2-blocker, or were unexposed was 3.6%, 5.5%, and 4.1% respectively.
A small prospective observational cohort study followed 113 women exposed to omeprazole during pregnancy (89% with first trimester exposures). The reported rate of major congenital malformations was 4% in the omeprazole group, 2% in controls exposed to non-teratogens, and 2.8% in disease paired controls. Rates of spontaneous and elective abortions, preterm deliveries, gestational age at delivery, and mean birth weight were similar among the groups.
Several studies have reported no apparent adverse short-term effects on the infant when single-dose oral or intravenous omeprazole was administered to over 200 pregnant women as premedication for cesarean section under general anesthesia.
Animal Data
Omeprazole
Reproductive studies conducted with omeprazole in rats at oral doses up to 138 mg/kg/day (about 34 times an oral human dose of 40 mg on a body surface area basis) and in rabbits at doses up to 69.1 mg/kg/day (about 34 times an oral human dose of 40 mg on a body surface area basis) during organogenesis did not disclose any evidence for a teratogenic potential of omeprazole. In rabbits, omeprazole in a dose range of 6.9 to 69.1 mg/kg/day (about 3.4 to 34 times an oral human dose of 40 mg on a body surface area basis) administered during organogenesis produced dose-related increases in embryo-lethality, fetal resorptions, and pregnancy disruptions. In rats, dose-related embryo/fetal toxicity and postnatal developmental toxicity were observed in offspring resulting from parents treated with omeprazole at 13.8 to 138.0 mg/kg/day (about 3.4 to 34 times an oral human dose of 40 mg on a body surface area basis), administered prior to mating through the lactation period.
Esomeprazole
No effects on embryo-fetal development were observed in reproduction studies with esomeprazole magnesium in rats at oral doses up to 280 mg/kg/day (about 68 times an oral human dose of 40 mg on a body surface area basis) or in rabbits at oral doses up to 86 mg/kg/day (about 41 times the human dose on a body surface area basis) administered during organogenesis.
A pre- and postnatal developmental toxicity study in rats with additional endpoints to evaluate bone development was performed with esomeprazole magnesium at oral doses of 14 to 280 mg/kg/day (about 3.4 to 68 times an oral human dose of 40 mg on a body surface area basis). Neonatal/early postnatal (birth to weaning) survival was decreased at doses equal to or greater than 138 mg/kg/day (about 34 times an oral human dose of 40 mg on a body surface area basis). Body weight and body weight gain were reduced and neurobehavioral or general developmental delays in the immediate post-weaning timeframe were evident at doses equal to or greater than 69 mg/kg/day (about 17 times an oral human dose of 40 mg on a body surface area basis). In addition, decreased femur length, width and thickness of cortical bone, decreased thickness of the tibial growth plate and minimal to mild bone marrow hypocellularity were noted at doses equal to or greater than 14 mg/kg/day (about 3.4 times an oral human dose of 40 mg on a body surface area basis). Physeal dysplasia in the femur was observed in offspring of rats treated with oral doses of esomeprazole magnesium at doses equal to or greater than 138 mg/kg/day (about 34 times an oral human dose of 40 mg on a body surface area basis).
Effects on maternal bone were observed in pregnant and lactating rats in a pre- and postnatal toxicity study when esomeprazole magnesium was administered at oral doses of 14 to 280 mg/kg/day (about 3.4 to 68 times an oral human dose of 40 mg on a body surface area basis). When rats were dosed from gestational day 7 through weaning on postnatal day 21, a statistically significant decrease in maternal femur weight of up to 14% (as compared to placebo treatment) was observed at doses equal to or greater than 138 mg/kg/day (about 34 times an oral human dose of 40 mg on a body surface area basis).
A pre- and postnatal development study in rats with esomeprazole strontium (using equimolar doses compared to esomeprazole magnesium study) produced similar results in dams and pups as described above.
A follow up developmental toxicity study in rats with further time points to evaluate pup bone development from postnatal day 2 to adulthood was performed with esomeprazole magnesium at oral doses of 280 mg/kg/day (about 68 times an oral human dose of 40 mg on a body surface area basis) where esomeprazole administration was from either gestational day 7 or gestational day 16 until parturition. When maternal administration was confined to gestation only, there were no effects on bone physeal morphology in the offspring at any age.

8.2 Lactation

Risk Summary
Esomeprazole is the S-isomer of omeprazole and limited data suggest that omeprazole may be present in human milk. There are no clinical data on the effects of esomeprazole on the breastfed infant or on milk production. The developmental and health benefits of breastfeeding should be considered along with the mother’s clinical need for esomeprazole and any potential adverse effects on the breastfed infant from esomeprazole or from the underlying maternal condition.

8.4 Pediatric Use

The safety and effectiveness of esomeprazole sodium for injection have been established in pediatric patients 1 month to 17 years of age for the short-term treatment of GERD with EE, as an alternative to oral therapy when oral esomeprazole is not possible or appropriate.
Use of esomeprazole sodium for injection in this age group is based on extrapolation of adult efficacy to children and the selection of dose based on exposure-matching of pediatrics to adults supported by the following evidence: a) results observed from a pharmacokinetic (PK) study on esomeprazole sodium for injection in pediatric patients, b) predictions from a population PK model comparing I.V. PK data between adult and pediatric patients, and c) relationship between exposure and pharmacodynamic results obtained from adult I.V. and pediatric oral data and d) PK results from adequate and well-controlled studies that supported the approval of esomeprazole sodium for injection in adults [see Adverse Reactions (6.1), Clinical Pharmacology (12.3), Clinical Studies (14.1)].
The safety and effectiveness of esomeprazole sodium for injection have not been established in patients less than 1 month of age for the treatment of GERD with EE or for risk reduction of rebleeding of gastric or duodenal ulcer following therapeutic endoscopy.
Juvenile Animal Data
In a juvenile rat toxicity study, esomeprazole was administered with both magnesium and strontium salts at oral doses about 34 to 68 times a daily human dose of 40 mg based on body surface area. Increases in death were seen at the high dose, and at all doses of esomeprazole, there were decreases in body weight, body weight gain, femur weight and femur length, and decreases in overall growth [see Nonclinical Toxicology (13.2)].

8.5 Geriatric Use

In a clinical trial of patients with bleeding gastric or duodenal ulcers, 52% of 375 patients randomized to esomeprazole sodium for injection were 65 years of age and over. No overall differences in safety and efficacy were observed between the elderly and younger individuals, and other reported clinical experience with esomeprazole sodium for injection and oral esomeprazole has not identified differences in responses between the elderly and younger patients, but greater sensitivity of some older individuals cannot be ruled out.

8.6 Hepatic Impairment

GERD with EE
Exposure to esomeprazole was increased substantially in patients with severe hepatic impairment (Child-Pugh Class C) but not in patients with mild to moderate hepatic impairment (Child-Pugh Classes A and B) compared to patients with normal liver function [see Clinical Pharmacology (12.3)].
For adult patients, no dosage adjustment is necessary for mild to moderate hepatic impairment. For patients with severe hepatic impairment the maximum recommended dosage is 20 mg once daily [see Dosage and Administration (2.3)].
Risk Reduction of Rebleeding of Gastric or Duodenal Ulcers following Therapeutic Endoscopy There are no pharmacokinetic data available for esomeprazole sodium for injection administered as continuous intravenous administration in patients with hepatic impairment. Exposure to intravenous omeprazole, of which esomeprazole is an enantiomer, increased in patients with all degrees of hepatic impairment compared to subjects with normal liver function [see Clinical Pharmacology (12.3)].
For adult patients, no dosage adjustment of the initial esomeprazole sodium for injection 80 mg loading dose is necessary for patients with any degree of hepatic impairment. Reduce the rate of the continuous infusion to 6 mg/hour for patients with mild to moderate liver impairment (Child-Pugh Classes A and B) and to 4 mg/hour for patients with severe hepatic impairment (Child-Pugh Class C) [see Dosage and Administration (2.3)].

10 OVERDOSAGE

The symptoms described in connection with deliberate esomeprazole overdose (limited experience of doses in excess of 240 mg/day) are transient. Reports of overdosage with omeprazole in humans may also be relevant. Doses ranged up to 2,400 mg (120 times the usual recommended clinical dose). Manifestations were variable, but included confusion, drowsiness, blurred vision, tachycardia, nausea, diaphoresis, flushing, headache, dry mouth, and other adverse reactions similar to those seen at recommended dosages. See the full prescribing information for oral omeprazole for complete safety information. No specific antidote for esomeprazole is known. Since esomeprazole is extensively protein bound, it is not expected to be removed by dialysis. In the event of overdosage, treatment should be symptomatic and supportive.
If over-exposure occurs, call your Poison Control Center at 1-800-222-1222 for current information on the management of poisoning or overdosage.

11 DESCRIPTION

The active ingredient in esomeprazole sodium for injection is (S)-5-methoxy-2[[(4-methoxy-3,5-dimethyl-2-pyridinyl)-methyl]sulfinyl]-1 H-benzimidazole sodium, a PPI. Esomeprazole is the S-isomer of omeprazole, which is a mixture of the S- and R-isomers. Its molecular formula is C17H18N3O3SNa with molecular weight of 367.4 g/mol (sodium salt) and 345.4 g/mol (parent compound). Esomeprazole sodium is a white or almost white, hygroscopic powder. It is very soluble in water and freely soluble in ethanol (95%). The structural formula is:

Esomeprazole sodium for injection is supplied as a sterile, freeze-dried, white to off-white, porous cake or powder in a 5 mL single-dose vial, intended for intravenous administration after reconstitution with 0.9% Sodium Chloride Injection, USP; Lactated Ringer’s Injection, USP or 5% Dextrose Injection, USP. Esomeprazole sodium for injection contains 40 mg esomeprazole (equivalent to 42.5 mg esomeprazole sodium), edetate disodium 1.5 mg and sodium hydroxide q.s. for pH adjustment. The pH of reconstituted solution of esomeprazole sodium for injection depends on the reconstitution volume and is in the pH range of 9 to 11. The stability of esomeprazole sodium in aqueous solution is strongly pH dependent. The rate of degradation increases with decreasing pH.

12 CLINICAL PHARMACOLOGY

12.1 Mechanism of Action

Esomeprazole belongs to a class of antisecretory compounds, the substituted benzimidazoles, that suppress gastric acid secretion by specific inhibition of the H^+/K^+ ATPase enzyme system at the secretory surface of the gastric parietal cell. Esomeprazole is protonated and converted in the acidic compartment of the parietal cell forming the active inhibitor, the achiral sulphenamide. Because this enzyme system is regarded as the acid (proton) pump within the gastric mucosa, esomeprazole has been characterized as a gastric acid-pump inhibitor, in that it blocks the final step of acid production. This effect is dose-related and leads to inhibition of both basal and stimulated acid secretion irrespective of the stimulus.

12.2 Pharmacodynamics

Antisecretory Activity

The effect of esomeprazole on 24-hour intragastric pH in healthy subjects was evaluated in two studies of 20 mg and 40 mg esomeprazole sodium for injection infused intravenously once daily over 30 minutes for 5 days, as shown in Table 7.

Table 7: Effect of Esomeprazole Sodium for Injection on Intragastric pH on Day 5
 | Esomeprazole sodium for injection 20 mg once daily (n=22) | Esomeprazole sodium for injection 40 mg once daily (n=38)
% Time Gastric pH>4 (95% CI) | 49.5 41.9 to 57.2 | 66.2 62.4 to 70.0

Gastric pH was measured over a 24-hour period
The effects of esomeprazole on 24-hour intragastric pH following administration of an intravenous infusion of 80 mg esomeprazole sodium for injection over 30 minutes followed by a continuous infusion of 8 mg/hour for 23.5 hours was evaluated in two studies.
In H. pylori-negative healthy Caucasian subjects (n=24), the % time over 24 hours (95% CI) when the intragastric pH was > 6 and > 7 was 52.3 % (40.3, 64.4) and 4.8 % (1.8, 7.8), respectively.
In H. pylori-positive (n=8) and H. pylori-negative (n=11) healthy Chinese subjects, the % time over 24 hours (95% CI) when intragastric pH was > 6 and > 7 was 53% (45.6, 60.3) and 15.1% (9.5, 20.7). The percentage of time with intragastric pH > 6 [59% vs. 47%] and with pH > 7 [17% vs. 11%] tended to be larger in the H. pylori positive subjects compared to H. pylori-negative subjects.
Serum Gastrin Effects
The effect of esomeprazole on serum gastrin concentrations was evaluated in approximately 2,700 patients in clinical trials of oral esomeprazole for up to 8 weeks and in over 1,300 patients treated for up to 12 months. The mean fasting gastrin level increased in a dose-related manner. The increase in serum gastrin concentrations reached a plateau within two to three months of therapy and returned to baseline levels within four weeks after discontinuation of therapy.
Increased gastrin causes enterochromaffin-like cell hyperplasia and increased serum Chromogranin A (CgA) levels. The increased CgA levels may cause false positive results in diagnostic investigations for neuroendocrine tumors [see Warnings and Precautions (5.9)].
Enterochromaffin-like (ECL) Cell Effects
There are no data available on the effects of intravenous esomeprazole on ECL cells.
Human gastric biopsy specimens have been obtained from more than 3,000 patients (both children and adults) treated orally with omeprazole in long-term clinical trials. The incidence of ECL cell hyperplasia in these studies increased with time; however, no case of ECL cell carcinoids, dysplasia, or neoplasia has been found in these patients [see Nonclinical Toxicology (13.1)].
In over 1,000 patients treated with oral esomeprazole (10 mg, 20 mg or 40 mg/day) for up to 12 months, the prevalence of ECL cell hyperplasia increased with time and dose. No patient developed ECL cell carcinoids, dysplasia, or neoplasia in the gastric mucosa.
Endocrine Effects
Esomeprazole had no effect on thyroid function when given in oral doses of 20 mg or 40 mg for 4 weeks. Other effects of esomeprazole on the endocrine system were assessed in studies of omeprazole. Oral doses of omeprazole 30 mg or 40 mg per day for 2 to 4 weeks had no effect on carbohydrate metabolism, circulating levels of parathyroid hormone, cortisol, estradiol, testosterone, prolactin, cholecystokinin or secretin.

12.3 Pharmacokinetics

Absorption
The pharmacokinetics of esomeprazole in healthy subjects following administration of esomeprazole sodium for injection 20 mg and 40 mg once daily as intravenous infusion over 30 minutes for 5 days are shown in Table 8.

Table 8: Geometric Mean (95% CI) Pharmacokinetic Parameters of Esomeprazole Sodium for Injection Following Dosing for 5 Days
Parameter | Esomeprazole sodium for injection 20 mg (n=24) | Esomeprazole sodium for injection 40 mg (n=38)
AUC (micromol*h/L) | 5.1 (4.0:6.6) | 16.2 (14.5:18.2)
Cmax (micromol/L)) | 3.9 (3.2:4.7) | 7.5 (6.9:8.1)
t1/2 (h) | 1.1 (0.9:1.2) | 1.4 (1.3:1.5)

Following intravenous administration of esomeprazole sodium for injection in 24 healthy subjects as a loading dose of 80 mg over 30 minutes followed by a continuous infusion of 8 mg/hour for 23.5 hours (for a total of 24 hours), esomeprazole pharmacokinetic parameters [geometric mean value (95% CI)] were as follows: AUCt 111.1 micromol*h/L (100.5, 122.7 micromol*h/L), Cmax 15.0 micromol/L (13.5, 16.6 micromol/L), and steady state plasma concentration (Css) 3.9 micromol/L (3.5, 4.5 micromol/L). In another study of healthy Caucasian subjects administered the same treatment regimen.
Esomeprazole is a time-dependent inhibitor of CYP2C19, resulting in autoinhibition and nonlinear pharmacokinetics. The systemic exposure increases in a more than dose proportional manner after multiple oral doses of esomeprazole. Compared to the first dose, the systemic exposure (Cmax and AUC0-24h) at steady state following once a day dosing increased by 43% and 90%, respectively, compared to after the first dose for the 20 mg dose and increased by 95% and 159%, respectively, for the 40 mg dose.
Distribution
Esomeprazole is 97% bound to plasma proteins. Plasma protein binding is constant over the concentration range of 2 to 20 micromol/L. The apparent volume of distribution at steady state in healthy subjects is approximately 16 L.
Elimination
Metabolism
Esomeprazole is extensively metabolized in the liver by the cytochrome P450 (CYP) enzyme system. The metabolites of esomeprazole lack antisecretory activity. The major part of esomeprazole’s metabolism is dependent upon the CYP2C19 isoenzyme, which forms the hydroxy and desmethyl metabolites. The remaining amount is dependent on CYP3A4 which forms the sulphone metabolite.
Excretion
Esomeprazole is excreted as metabolites primarily in urine but also in feces. Less than 1% of parent drug is excreted in the urine. Esomeprazole is completely eliminated from plasma, and there is no accumulation during once daily administration. The plasma elimination half-life of esomeprazole following intravenous administration of esomeprazole sodium for injection is approximately 1.1 to 1.4 hours and is prolonged with increasing doses.
The plasma clearance (CL) is approximately 5.9 to 7.2 L/h during administration of esomeprazole sodium for injection as an intravenous infusion of 80 mg over 30 minutes followed by a continuous infusion of 8 mg/hour for 23.5 hours.
Specific Populations
Geriatric Patients
The AUC and Cmax values of esomeprazole were slightly higher (25% and 18%, respectively) in the elderly as compared to younger subjects at steady state. This increase in exposure is not considered clinically relevant.
Pediatric Patients
The pharmacokinetics of esomeprazole were evaluated in 50 pediatric patients birth to 17 years of age, inclusive (of which 44 pediatric patients were 1 month to 17 years) in a randomized, open-label, multi-national, multiple dose study of 20 mg esomeprazole sodium for injection administered as a once-daily 3-minute intravenous injection. Esomeprazole plasma AUC values were 183% and 60% higher in pediatric patients aged 6 to 11 years and 12 to 17 years, respectively, compared to adults.
Subsequent pharmacokinetic analyses predicted the following dosage regimens would achieve comparable steady-state plasma exposures (AUC0-24) to those observed in adult patients administered 20 mg of esomeprazole sodium for injection once daily: 0.5 mg/kg once daily for pediatric patients 1 month to 11 months of age, 10 mg once daily for pediatric patients 1 year to 17 years with body weight less than 55 kg, and 20 mg once daily for pediatric patients 1 year to 17 years with body weight of 55 kg and greater. Increasing the infusion duration from 3 minutes to 10 minutes or 30 minutes was predicted to produce steady-state Cmax values that were comparable to those observed in adult patients at the 40 mg and 20 mg esomeprazole sodium for injection doses, respectively [see Use in Specific Populations (8.4)].
Male and Female Patients
The AUC and Cmax values of esomeprazole were slightly higher (13%) in females than in males at steady state when dosed orally. Similar differences have been seen for intravenous administration of esomeprazole. This increase in exposure is not considered clinically relevant.
Patients with Renal Impairment
The pharmacokinetics of esomeprazole in patients with renal impairment are not expected to be altered relative to healthy subjects as less than 1% of esomeprazole is excreted unchanged in urine.
Patients with Hepatic Impairment
The steady state pharmacokinetics of esomeprazole obtained after administration of 40 mg orally once daily to 4 patients each with mild (Child-Pugh Class A), moderate (Child-Pugh Class B), and severe (Child-Pugh Class C) hepatic impairment were compared to those obtained in 36 male and female GERD patients with normal liver function. In patients with mild and moderate hepatic impairment, the AUCs were within the range that could be expected in patients with normal liver function. In patients with severe hepatic impairment, the AUCs were 2 to 3 times higher than in the patients with normal liver function [see Use in Specific Populations (8.6)].
There are no pharmacokinetic data available for esomeprazole administered as continuous intravenous administration in patients with liver impairment. The pharmacokinetics of intravenous omeprazole 80 mg infused over 30 minutes, followed by 8 mg/hour over 47.5 hours in patients with mild (Child-Pugh Class A; n=5), moderate (Child-Pugh Class B; n=4) and severe (Child-Pugh Class C; n=3) liver impairment were compared to those obtained in 24 male and female healthy subjects. In patients with mild and moderate liver impairment, omeprazole clearance and steady state plasma concentration was approximately 35% lower and 50% higher, respectively, than in healthy subjects. In patients with severe liver impairment, the omeprazole clearance was 50% of that in healthy subjects and the steady state plasma concentration was double that in healthy subjects [see Use in Specific Populations (8.6)].
Drug Interaction Studies
Effect of Esomeprazole/Omeprazole on Other Drugs
In vitro and in vivo studies have shown that esomeprazole is not likely to inhibit CYPs 1A2, 2A6, 2C9, 2D6, 2E1 and 3A4.
Antiretrovirals
For some antiretroviral drugs, such as rilpivirine, atazanavir and nelfinavir, decreased serum concentrations have been reported when given together with omeprazole [see Drug Interactions (7)].
Rilpivirine:
Following multiple doses of rilpivirine (150 mg, daily) and omeprazole (20 mg, daily), AUC was decreased by 40%, Cmax by 40%, and Cmin by 33% for rilpivirine [see Contraindications (4)].
Nelfinavir:
Following multiple doses of nelfinavir (1,250 mg, twice daily) and omeprazole (40 mg daily), AUC was decreased by 36% and 92%, Cmax by 37% and 89% and Cmin by 39% and 75% respectively for nelfinavir and M8.
Atazanavir:
Following multiple doses of atazanavir (400 mg, daily) and omeprazole (40 mg, daily, 2 hours before atazanavir), AUC was decreased by 94%, Cmax by 96%, and Cmin by 95%.
Saquinavir:
Following multiple dosing of saquinavir/ritonavir (1,000/100 mg) twice daily for 15 days with omeprazole 40 mg daily co-administered days 11 to 15. The AUC was increased by 82%, Cmax by 75%, and Cmin by 106%. The mechanism behind this interaction is not fully elucidated.
Clopidogrel
In a crossover study, healthy subjects were administered clopidogrel (300 mg loading dose followed by 75 mg per day as the maintenance dosage for 28 days) alone and with esomeprazole (40 mg orally once daily at the same time as clopidogrel) for 29 days. Exposure to the active metabolite of clopidogrel was reduced by 35% to 40% over this time period when clopidogrel and esomeprazole were administered together. Pharmacodynamic parameters were also measured and demonstrated that the change in inhibition of platelet aggregation was related to the change in the exposure to clopidogrel active metabolite [see Warnings and Precautions (5.7), Drug Interactions (7)].
Mycophenolate Mofetil
Administration of omeprazole 20 mg twice daily for 4 days and a single 1,000 mg dose of MMF approximately one hour after the last dose of omeprazole to 12 healthy subjects in a cross-over study resulted in a 52% reduction in the Cmax and 23% reduction in the AUC of MPA [see Drug Interactions (7)].
Cilostazol
Omeprazole acts as an inhibitor of CYP2C19. Omeprazole, given in doses of 40 mg daily for one week to 20 healthy subjects in cross-over study, increased Cmax and AUC of cilostazol by 18% and 26% respectively. The Cmax and AUC of one of the active metabolites, 3,4-dihydro-cilostazol, which has 4 to 7 times the activity of cilostazol, were increased by 29% and 69%, respectively. Co-administration of cilostazol with omeprazole is expected to increase concentrations of cilostazol and the above mentioned active metabolite [see Drug Interactions (7)].
Diazepam
Co-administration of esomeprazole 30 mg and diazepam, a CYP2C19 substrate, resulted in a 45% decrease in clearance of diazepam. Increased plasma levels of diazepam were observed 12 hours after dosing and onwards. However, at that time, the plasma levels of diazepam were below the therapeutic interval, and thus this interaction is unlikely to be of clinical relevance.
Digoxin
Concomitant administration of omeprazole 20 mg once daily and digoxin in healthy subjects increased the bioavailability of digoxin by 10% (30% in two subjects) [see Drug Interactions (7)].
Other Drugs
Concomitant administration of esomeprazole and either naproxen (non-selective NSAID) did not identify any clinically relevant changes in the pharmacokinetic profiles of these NSAIDs.
Effect of Other Drugs on Esomeprazole/Omeprazole
St. John’s Wort
In a cross-over study in 12 healthy male subjects, St. John’s Wort (300 mg three times daily for 14 days) significantly decreased the systemic exposure of omeprazole in CYP2C19 poor metabolizers (Cmax and AUC decreased by 37.5% and 37.9%, respectively) and extensive metabolizers (Cmax and AUC decreased by 49.6% and 43.9%, respectively) [see Drug Interactions (7)].
Voriconazole
Concomitant administration of omeprazole and voriconazole (a combined inhibitor of CYP2C19 and CYP3A4) resulted in more than doubling of the omeprazole exposure. When voriconazole (400 mg every 12 hours for one day, followed by 200 mg once daily for 6 days) was given with omeprazole (40 mg once daily for 7 days) to healthy subjects, the steady-state Cmax and AUC0-24 of omeprazole significantly increased: an average of 2 times (90% CI: 1.8, 2.6) and 4 times (90% CI: 3.3, 4.4), respectively, as compared to when omeprazole was given without voriconazole [see Drug Interactions (7)].
Other Drugs
Co-administration of esomeprazole with oral contraceptives, diazepam, phenytoin, quinidine, naproxen (non-selective NSAID) did not seem to change the pharmacokinetic profile of esomeprazole.

12.4 Microbiology

Effects on Gastrointestinal Microbial Ecology
Decreased gastric acidity due to any means including proton pump inhibitors, increases gastric counts of bacteria normally present in the gastrointestinal tract. Treatment with proton pump inhibitors may lead to slightly increased risk of gastrointestinal infections such as Salmonella and Campylobacter and, in hospitalized patients, possibly also Clostridium difficile.

12.5 Pharmacogenomics

CYP2C19, a polymorphic enzyme, is involved in the metabolism of esomeprazole. The CYP2C19*1 allele is fully functional while the CYP2C19*2 and *3 alleles are nonfunctional. There are other alleles associated with no or reduced enzymatic function. Patients carrying two fully functional alleles are extensive metabolizers and those carrying two loss-of-function alleles are poor metabolizers. The systemic exposure to esomeprazole varies with a patient’s metabolism status: poor metabolizers > intermediate metabolizers > extensive metabolizers. Approximately 3% of Caucasians and 15 to 20% of Asians are CYP2C19 poor metabolizers.
Systemic esomeprazole exposures were modestly higher (approximately 17%) in CYP2C19 intermediate metabolizers (IM; n=6) compared to extensive metabolizers (EM; n=17) of CYP2C19. Similar pharmacokinetic differences were noted across these genotypes in a study of Chinese healthy subjects that included 7 EMs and 11 IMs. There is very limited pharmacokinetic information for poor metabolizers (PM) from these studies.
At steady state following once daily administration of esomeprazole sodium for injection, 40 mg, the ratio of AUC in Poor Metabolizers to AUC in the rest of the population (EMs) is approximately 1.5. This change in exposure is not considered clinically meaningful.

13 NONCLINICAL TOXICOLOGY

13.1 Carcinogenesis, Mutagenesis, Impairment of Fertility

The carcinogenic potential of esomeprazole was assessed using omeprazole studies. In two 24-month oral carcinogenicity studies in rats, omeprazole at daily doses of 1.7, 3.4, 13.8, 44.0, and 140.8 mg/kg/day (about 0.4 to 34 times the human dose of 40 mg/day expressed on a body surface area basis) produced gastric ECL cell carcinoids in a dose-related manner in both male and female rats; the incidence of this effect was markedly higher in female rats, which had higher blood levels of omeprazole. Gastric carcinoids seldom occur in the untreated rat. In addition, ECL cell hyperplasia was present in all treated groups of both sexes. In one of these studies, female rats were treated with 13.8 mg omeprazole/kg/day (about 3.4 times the human dose of 40 mg/day on a body surface area basis) for 1 year, then followed for an additional year without the drug. No carcinoids were seen in these rats. An increased incidence of treatment-related ECL cell hyperplasia was observed at the end of 1 year (94% treated vs 10% controls). By the second year the difference between treated and control rats was much smaller (46% vs 26%) but still showed more hyperplasia in the treated group. Gastric adenocarcinoma was seen in one rat (2%). No similar tumor was seen in male or female rats treated for 2 years. For this strain of rat no similar tumor has been noted historically, but a finding involving only one tumor is difficult to interpret. A 78-week oral mouse carcinogenicity study of omeprazole did not show increased tumor occurrence, but the study was not conclusive.
Esomeprazole was negative in the Ames mutation test, in the in vivo rat bone marrow cell chromosome aberration test, and the in vivo mouse micronucleus test. Esomeprazole, however, was positive in the in vitro human lymphocyte chromosome aberration test. Omeprazole was positive in the in vitro human lymphocyte chromosome aberration test, the in vivo mouse bone marrow cell chromosome aberration test, and the in vivo mouse micronucleus test.
The potential effects of esomeprazole on fertility and reproductive performance were assessed using omeprazole studies. Omeprazole at oral doses up to 138 mg/kg/day in rats (about 34 times the human dose of 40 mg/day on a body surface area basis) was found to have no effect on reproductive performance of parental animals.

13.2 Animal Toxicology and/or Pharmacology

Reproduction Studies
Reproduction studies have been performed in rats at oral doses up to 280 mg/kg/day (about 68 times an oral human dose of 40 mg on a body surface area basis) and in rabbits at oral doses up to 86 mg/kg/day (about 42 times an oral human dose of 40 mg on a body surface area basis) and have revealed no evidence of impaired fertility or harm to the fetus due to esomeprazole [see Use in Specific Populations (8.1)].
Juvenile Animal Study
A 28-day toxicity study with a 14-day recovery phase was conducted in juvenile rats with esomeprazole magnesium at doses of 70 to 280 mg/kg/day (about 17 to 68 times a daily oral human dose of 40 mg on a body surface area basis). An increase in the number of deaths at the high dose of 280 mg/kg/day was observed when juvenile rats were administered esomeprazole magnesium from postnatal day 7 through postnatal day 35. In addition, doses equal to or greater than 140 mg/kg/day (about 34 times a daily oral human dose of 40 mg on a body surface area basis), produced treatment-related decreases in body weight (approximately 14%) and body weight gain, decreases in femur weight and femur length, and affected overall growth. Comparable findings described above have also been observed in this study with another esomeprazole salt, esomeprazole strontium, at equimolar doses of esomeprazole.

14 CLINICAL STUDIES

14.1 Acid Suppression in GERD

Four multicenter, open-label, two-period crossover studies were conducted to compare the pharmacodynamic effects of esomeprazole following intravenous or oral administration on acid suppression in 206 patients with symptoms of GERD with or without erosive esophagitis. Patients were randomized to receive either 20 or 40 mg of esomeprazole sodium for injection or oral esomeprazole once daily for 10 days (Period 1), and then were switched in Period 2 to the other formulation for 10 days, matching their respective dose from Period 1. Esomeprazole sodium for injection, 20 mg and 40 mg was administered as a 3-minute injection in two of the studies and as a 15-minute infusion in the other two studies.
The patient population ranged from 18 to 72 years old; 54% were female; 53% Caucasian, 24% Black, 5% Asian, and 17% other race. Basal acid output (BAO) and maximal acid output (MAO) were determined 22 to 24 hours post-dose on Period 1, Day 11; on Period 2, Day 3; and on Period 2, Day 11. BAO and MAO were estimated from 1-hour continuous collections of gastric contents prior to and following (respectively) subcutaneous injection of 6.0 mcg/kg of pentagastrin.
In these studies, after 10 days of once daily administration, esomeprazole sodium for injection, 20 mg and 40 mg were similar to the corresponding oral dosage of esomeprazole in their ability to suppress BAO and MAO in these GERD patients (see Table 9 below).
There were no major changes in acid suppression when switching between intravenous and oral dosage forms.

Table 9: Mean (SD) BAO and MAO Measured 22 to 24 Hours Post-Dose Following Once Daily Oral and Intravenous Administration of Esomeprazole for 10 days in GERD Patients with or without a History of EE
Study | Dose in mg | Intravenous Administration Method | BAO in mmol H^+/h |  | MAO in mmol H^+/h
Study | Dose in mg | Intravenous Administration Method | Intravenous | Oral | Intravenous | Oral
1 (N=42) | 20 | 3-minute injection | 0.71 (1.24) | 0.69 (1.24) | 5.96 (5.41) | 5.27 (5.39)
2 (N=44) | 20 | 15-minute infusion | 0.78 (1.38) | 0.82 (1.34) | 5.95 (4.00) | 5.26 (4.12)
3 (N=50) | 40 | 3-minute injection | 0.36 (0.61) | 0.31 (0.55) | 5.06 (3.90) | 4.41 (3.11)
4 (N=47) | 40 | 15-minute infusion | 0.36 (0.79) | 0.22 (0.39) | 4.74 (3.65) | 3.52 (2.86)

14.2 Bleeding Gastric or Duodenal Ulcers

A randomized, double blind, placebo-controlled clinical study was conducted in 764 patients who presented with endoscopically confirmed gastric or duodenal ulcer bleeding. The population was 18 to 98 years old; 68% were male, 87% Caucasian, 1% Black, 7% Asian, and 4% other race. Following endoscopic hemostasis, patients were randomized to either placebo or esomeprazole sodium for injection, 80 mg as an intravenous infusion over 30 minutes followed by a continuous infusion of 8 mg/hour for a total of 72 hours. After the initial 72-hour period, all patients received an oral PPI for 27 days. The occurrence of rebleeding within 3 days of randomization was 5.9% in the esomeprazole sodium for injection treated group compared to 10.3% for the placebo group (treatment difference -4.4%; 95% confidence interval: -8.3%, -0.6%; p=0.03). This treatment difference was similar to that observed at Day 7 and Day 30, during which all patients were receiving an oral PPI.
A randomized, double blind, placebo-controlled single-center study conducted in Hong Kong also demonstrated a reduction compared to placebo in the risk of rebleeding within 72 hours in patients with bleeding gastric or duodenal ulcers who received racemic omeprazole, 50% of which is the S-enantiomer esomeprazole.

16 HOW SUPPLIED/STORAGE AND HANDLING

Esomeprazole sodium for injection is supplied as a sterile, freeze-dried, white to off-white, porous cake or powder containing 40 mg of esomeprazole per single-dose vial.
40 mg per vial:
Single-Dose Vials in a Carton of 10 (each vial contains 40 mg of esomeprazole) NDC 55150-185-05
Storage
Store at 20° to 25°C (68° to 77°F) [see USP Controlled Room Temperature]. Protect from light. Store in carton until time of use.
Following reconstitution and administration, discard any unused portion of esomeprazole solution [see Dosage and Administration (2.4, 2.5)].
The vial stopper is not made with natural rubber latex.

17 PATIENT COUNSELING INFORMATION

Adverse Reactions
Advise patients to report to their healthcare provider if they experience any signs or symptoms consistent with:

- Hypersensitivity Reactions [see Contraindications (4)]
- Acute Tubulointerstitial Nephritis [see Warnings and Precautions (5.2)]
- Clostridium difficile-Associated Diarrhea [see Warnings and Precautions (5.3)]
- Bone Fracture [see Warnings and Precautions (5.4)]
- Severe Cutaneous Adverse Reactions [see Warnings and Precautions (5.5)]
- Cutaneous and Systemic Lupus Erythematosus [see Warnings and Precautions (5.6)]
- Hypomagnesemia and Mineral Metabolism [see Warnings and Precautions (5.8)]

Drug Interactions
Advise patients to report to their healthcare provider before they start treatment with any of the following:

- Rilpivirine-containing products [see Contraindications (4)]
- Clopidogrel [see Warnings and Precautions (5.7)]
- St. John’s Wort or rifampin [see Warnings and Precautions (5.9)]
- High-dose methotrexate [see Warnings and Precautions (5.11)]

Administration

- Inform patients that antacids may be used while taking esomeprazole sodium for injection.

Distributed by:
Eugia US LLC
279 Princeton-Hightstown Rd.
E. Windsor, NJ 08520
Manufactured by:
Eugia Pharma Specialities Limited
Hyderabad – 500032
India

PACKAGE LABEL-PRINCIPAL DISPLAY PANEL - 40 mg per vial - Container Label

Rx only NDC 55150-185-05
Esomeprazole
Sodium for Injection
40 mg per vial*
For Intravenous
Use Only.
Discard unused portion.
Sterile Single-Dose Vial

PACKAGE LABEL-PRINCIPAL DISPLAY PANEL - 40 mg per vial - Container-Carton (10 Vials)

Rx only NDC 55150-185-05
Esomeprazole
Sodium for Injection
40 mg per vial*
For Intravenous Use Only.
Discard unused portion.
Sterile 10 Single-Dose Vials
eugia